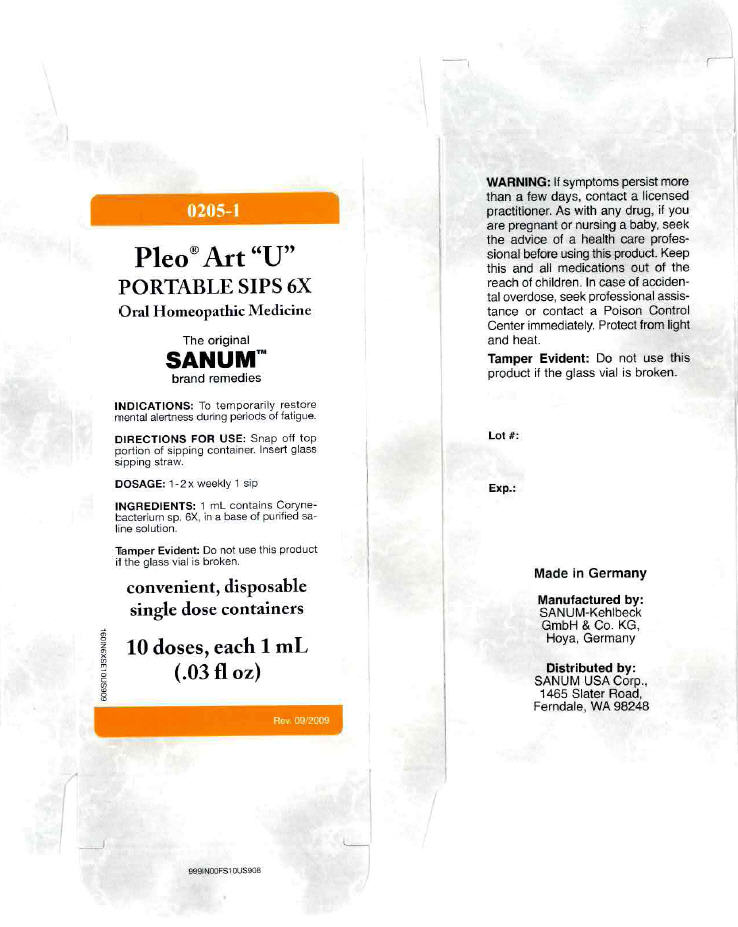 DRUG LABEL: Pleo Art U
NDC: 60681-0205 | Form: LIQUID
Manufacturer: Sanum Kehlbeck GmbH & Co. KG
Category: homeopathic | Type: HUMAN OTC DRUG LABEL
Date: 20120307

ACTIVE INGREDIENTS: Brevibacterium stationis 6 [hp_X]/1 mL
INACTIVE INGREDIENTS: water; sodium chloride

Pleo™ Art "U"
PORTABLE SIPS 6X

Oral Homeopathic Medicine

50 doses, each 1 mL
(.03 fl oz)

INDICATIONS

PURPOSE

To temporarily restore mental alertness during periods of fatigue.

DIRECTIONS FOR USE

Snap off top portion of sipping container. Insert glass sipping straw.

DOSAGE

1-2 × weekly 1 sip

INGREDIENTS

INACTIVE INGREDIENT

1 mL contains Corynebacterium sp. 6X, in a base of purified saline solution.

WARNING

If symptoms persist more than a few days, contact a licensed practitioner. As with any drug, if you are pregnant or nursing a baby, seek the advice of a health care professional before using this product.

KEEP OUT OF REACH OF CHILDREN

Keep this and all medications out of the reach of children. In case of accidental overdose, seek professional assistance or contact a Poison Control Center immediately.

STORAGE AND HANDLING

Protect from light and heat.

Tamper Evident

Do not use this product if the glass vial is broken or if imprinted security strip on carton is torn.

Made in Germany

Distributed by:
SANUM USA Corp.
1465 Slater Road
Ferndale, WA 98248

Manufactured By:
Sanum-Kehlbeck GmbH & Co. KG

Rev. 11/97

PRINCIPAL DISPLAY PANEL - 1 mL Vial Carton

0205-1

Pleo® Art "U"
PORTABLE SIPS 6X

Oral Homeopathic Medicine

The Original
SANUM™
brand remedies

INDICATIONS: To temporarily restore
mental alertness during periods of fatigue.

DIRECTIONS FOR USE: Snap off top
portion of sipping container. Insert glass
sipping straw.

DOSAGE: 1-2 × weekly 1 sip

INGREDIENTS: 1 mL contains Coryne-
bacterium sp. 6X, in a base of purified sa-
line solution.

Tamper Evident: Do not use this product
if the glass vial is broken.

convenient, disposable
single dose containers

10 doses, each 1 mL
(.03 fl oz)

Rev. 09/2009